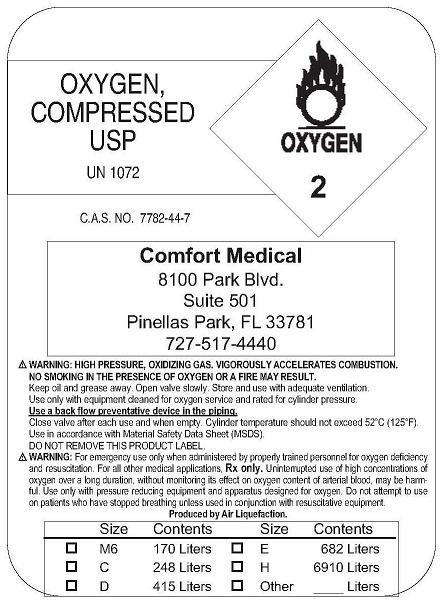 DRUG LABEL: Oxygen
NDC: 49799-0001 | Form: GAS
Manufacturer: Comfort Medical
Category: prescription | Type: HUMAN PRESCRIPTION DRUG LABEL
Date: 20091001

ACTIVE INGREDIENTS: Oxygen 99 L/100 L

Oxygen